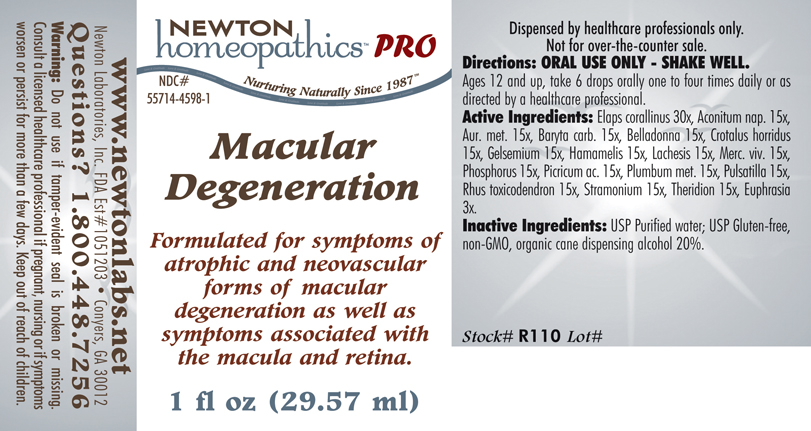 DRUG LABEL: Macular Degeneration 
NDC: 55714-4598 | Form: LIQUID
Manufacturer: Newton Laboratories, Inc.
Category: homeopathic | Type: HUMAN PRESCRIPTION DRUG LABEL
Date: 20110601

ACTIVE INGREDIENTS: Micrurus Corallinus Venom 30 [hp_X]/1 mL; Aconitum Napellus 15 [hp_X]/1 mL; Gold 15 [hp_X]/1 mL; Barium Carbonate 15 [hp_X]/1 mL; Atropa Belladonna 15 [hp_X]/1 mL; Crotalus Horridus Horridus Venom 15 [hp_X]/1 mL; Gelsemium Sempervirens Root 15 [hp_X]/1 mL; Hamamelis Virginiana Root Bark/stem Bark 15 [hp_X]/1 mL; Lachesis Muta Venom 15 [hp_X]/1 mL; Mercury 15 [hp_X]/1 mL; Phosphorus 15 [hp_X]/1 mL; Picric Acid 15 [hp_X]/1 mL; Lead 15 [hp_X]/1 mL; Pulsatilla Vulgaris 15 [hp_X]/1 mL; Toxicodendron Pubescens Leaf 15 [hp_X]/1 mL; Datura Stramonium 15 [hp_X]/1 mL; Theridion Curassavicum 15 [hp_X]/1 mL; Euphrasia Stricta 3 [hp_X]/1 mL
INACTIVE INGREDIENTS: Alcohol

Macular Degeneration

INDICATIONS & USAGE SECTION

Macular Degeneration Formulated for symptoms of atrophic and neovascular forms of macular degeneration as well as symptoms associated with the macula and retina.

DOSAGE & ADMINISTRATION SECTION

Directions: ORAL USE ONLY - SHAKE WELL. Ages 12 and up, take 6 drops orally one to four times daily or as directed by a healthcare professional.

ACTIVE INGREDIENT SECTION

Elaps corallinus 30x, Aconitum nap. 15x, Aur. met. 15x, Baryta carb. 15x, Belladonna 15x, Crotalus horridus 15x, Gelsemium 15x, Hamamelis 15x, Lachesis 15x, Merc. viv. 15x, Phosphorus 15x, Picricum ac. 15x, Plumbum met. 15x, Pulsatilla 15x, Rhus toxicodendron 15x, Stramonium 15x, Theridion 15x, Euphrasia 3x.

PURPOSE SECTION

Formulated for symptoms of atrophic and neovascular forms of macular degeneration as well as symptoms associated with the macula and retina.

INACTIVE INGREDIENT SECTION

Inactive Ingredients: USP Purified Water; USP Gluten-free, non-GMO, organic cane dispensing alcohol 20%.

QUESTIONS? SECTION

www.newtonlabs.net Newton Laboratories, Inc. FDA Est # 1051203 - Conyers, GA 30012
Questions? 1.800.448.7256

WARNINGS SECTION

Warning: Do not use if tamper - evident seal is broken or missing. Consult a licensed healthcare professional if pregnant, nursing or if symptoms worsen or persist for more than a few days. Keep out of reach of children.

PREGNANCY OR BREAST FEEDING SECTION

Consult a licensed healthcare professional if pregnant, nursing or if symptoms worsen or persist for more than a few days.

KEEP OUT OF REACH OF CHILDREN SECTION

Keep out of reach of children.